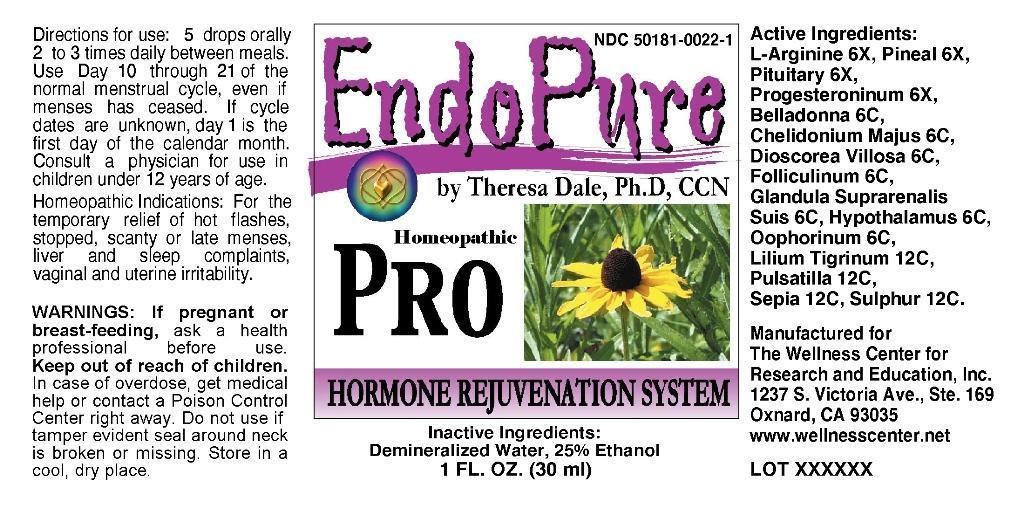 DRUG LABEL: EndoPure Pro
NDC: 50181-0022 | Form: LIQUID
Manufacturer: The Wellness Center
Category: homeopathic | Type: HUMAN OTC DRUG LABEL
Date: 20250529

ACTIVE INGREDIENTS: ARGININE 6 [hp_X]/1 mL; SUS SCROFA PINEAL GLAND 6 [hp_X]/1 mL; SUS SCROFA PITUITARY GLAND, POSTERIOR 6 [hp_X]/1 mL; PROGESTERONE 6 [hp_X]/1 mL; ATROPA BELLADONNA WHOLE 6 [hp_C]/1 mL; CHELIDONIUM MAJUS 6 [hp_C]/1 mL; DIOSCOREA VILLOSA TUBER 6 [hp_C]/1 mL; ESTRONE 6 [hp_C]/1 mL; SUS SCROFA ADRENAL GLAND 6 [hp_C]/1 mL; SUS SCROFA HYPOTHALAMUS 6 [hp_C]/1 mL; SUS SCROFA OVARY 6 [hp_C]/1 mL; LILIUM LANCIFOLIUM WHOLE FLOWERING 12 [hp_C]/1 mL; PULSATILLA VULGARIS 12 [hp_C]/1 mL; SEPIA OFFICINALIS JUICE 12 [hp_C]/1 mL; SULFUR 12 [hp_C]/1 mL
INACTIVE INGREDIENTS: WATER; ALCOHOL

Drug Facts

ACTIVE INGREDIENTS

L-Arginine 6X, Pineal (Suis) 6X, Pituitary (Suis) 6X, Progesteroninum 6X, Belladonna 6C, Chelidonium Majus 6C, Dioscorea Villosa 6C, Folliculinum 6C, Glandula Suprarenalis Suis 6C, Hypothalamus (Suis) 6C, Oophorinum (Suis) 6C, Lilium Tigrinum 12C, Pulsatilla 12C, Sepia 12C, Sulphur 12C

INDICATIONS

For the temporary relief of hot flashes, stopped, scanty or late menses, liver and sleep complaints, vaginal and uterine irritability.

WARNINGS

If pregnant or breast-feeding, ask a health professional before use. Keep out of reach of children. In case of overdose, get medical help or contact a Poison Control Center right away. Do not use if tamper evident seal around neck is broken or missing. Store in a cool, dry place.

DIRECTIONS

5 drops orally 2 to 3 times daily between meals. Use Day 10 through 21 of the normal menstral cycle, even if menses has ceased. If cycle dates are unknown, day 1 is the first day of the calender month. Consult a physician for use in children under 12 years of age.

INACTIVE INGREDIENTS

Demineralized Water, 25% Ethanol

KEEP OUT OF REACH OF CHILDREN

In case of overdose, get medical help or contact a Poison Control Center right away.

INDICATIONS AND USAGE

For the temporary relief of hot flashes, stopped, scanty or late menses, liver and sleep complaints, vaginal and uterine irritability.

QUESTIONS

Manufactured for

The Wellness Center for Research and Eduction, Inc.

1237 S. Victoria Ave., Ste. 169

Oxnard, CA 93035

www.wellnesscenter.net

PACKAGE LABEL

NDC 50181-0022-1

EndoPure

by Theresa Dale, Ph.D, CCN

Homeopathic

PRO

HORMONE REJUVENATION SYSTEM

1 FL. OZ. (30 ml)